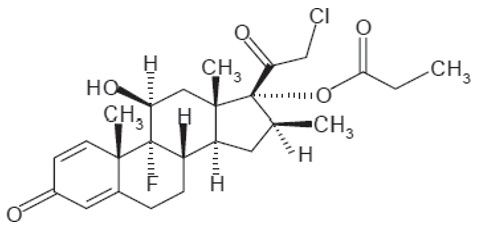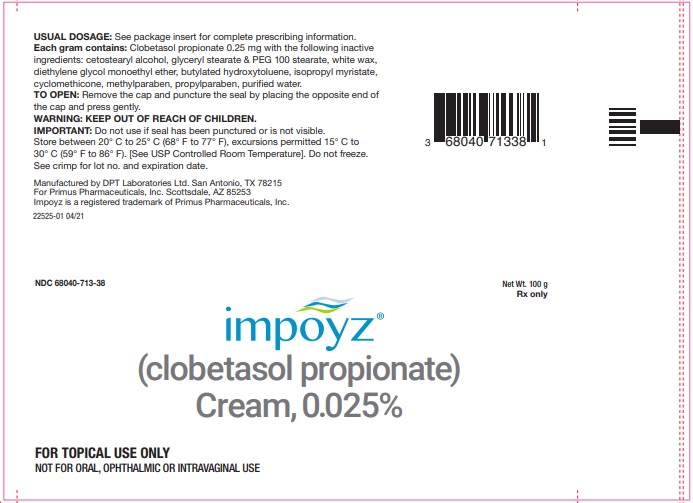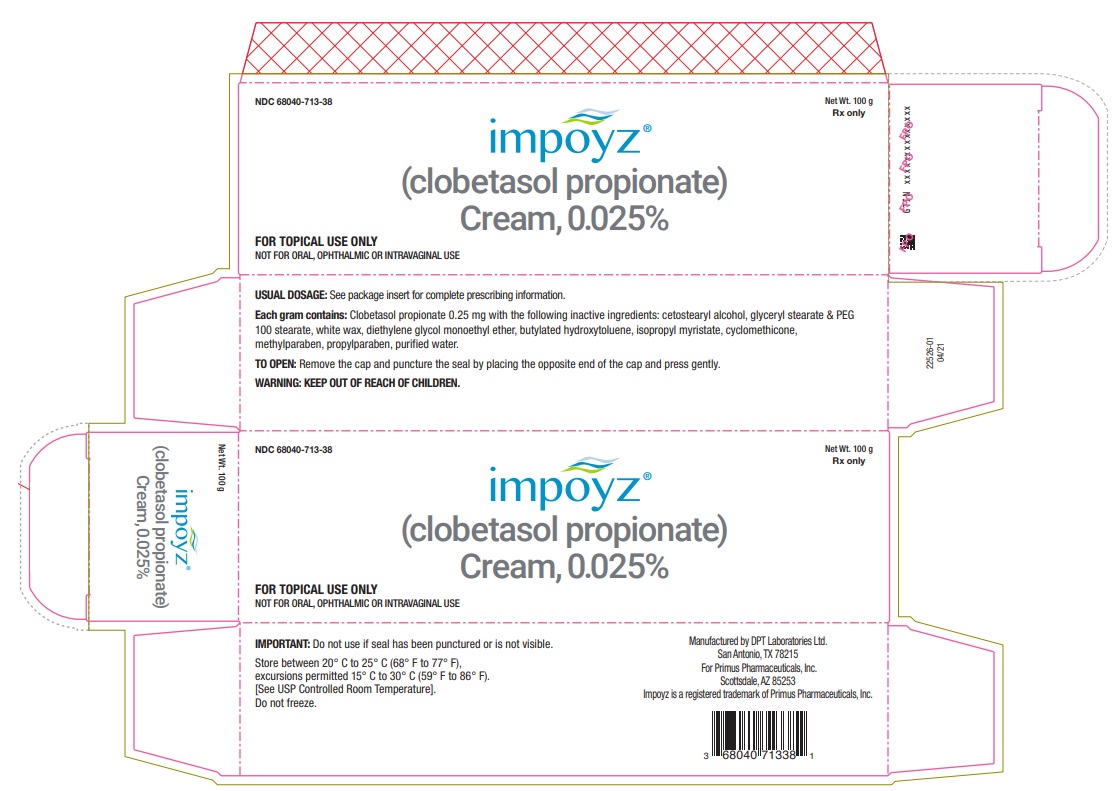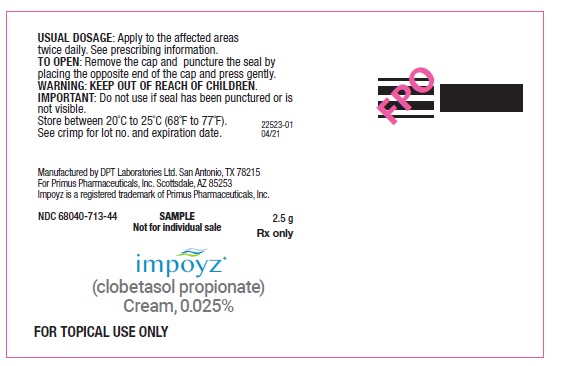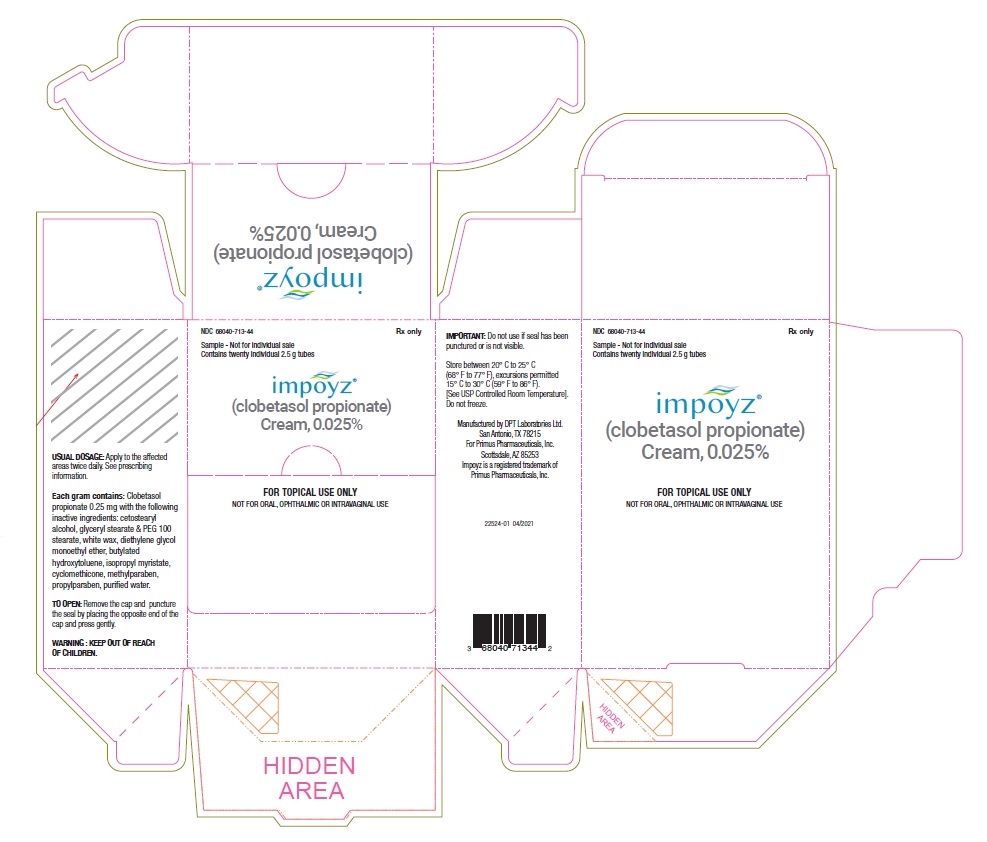 DRUG LABEL: Impoyz
NDC: 68040-713 | Form: CREAM
Manufacturer: Primus Pharmaceuticals, Inc.
Category: prescription | Type: HUMAN PRESCRIPTION DRUG LABEL
Date: 20240130

ACTIVE INGREDIENTS: CLOBETASOL PROPIONATE 0.25 mg/1 g
INACTIVE INGREDIENTS: BUTYLATED HYDROXYTOLUENE; CETOSTEARYL ALCOHOL; CYCLOMETHICONE; DIETHYLENE GLYCOL MONOETHYL ETHER; GLYCERYL STEARATE SE; PEG-100 STEARATE; ISOPROPYL MYRISTATE; METHYLPARABEN; PROPYLPARABEN; WATER; WHITE WAX

HIGHLIGHTS OF PRESCRIBING INFORMATION

These highlights do not include all the information needed to use IMPOYZ® Cream safely and effectively. See full prescribing information for IMPOYZ Cream.
IMPOYZ (clobetasol propionate) Cream, 0.025%, for topical use
Initial U.S. Approval: 1985

1 INDICATIONS AND USAGE

IMPOYZ Cream is a corticosteroid indicated for the treatment of moderate to severe plaque psoriasis in patients 18 years of age or older (1)

2 DOSAGE AND ADMINISTRATION

- Apply a thin layer of IMPOYZ Cream to the affected skin areas twice daily and rub in gently and completely. Wash hands after each application. Use IMPOYZ Cream for up to 2 consecutive weeks of treatment. (2)
- Discontinue IMPOYZ Cream when control is achieved. (2)
- The total dosage should not exceed 50 g per week. (2)
- Do not use if atrophy is present at the treatment site. (2)
- Do not bandage, cover, or wrap the treated skin areas unless directed by a physician. (2)
- Avoid use on the face scalp, axilla, groin, or other intertriginous areas. (2)
- IMPOYZ Cream is for topical use only. It is not for oral, ophthalmic, or intravaginal use. (2)

3 DOSAGE FORMS AND STRENGTHS

Cream, 0.025% (3)

4 CONTRAINDICATIONS

None (4)

5 WARNINGS AND PRECAUTIONS

- Clobetasol propionate has been shown to suppress the HPA axis at the dose tested. (5.1)
- Cushing’s syndrome, hyperglycemia, and glucosuria can also result from systemic absorption of topical corticosteroids. (5.1)
- Systemic absorption may require periodic evaluation for HPA axis suppression. Modify use if HPA axis develops. (5.1)
- Children may be more susceptible to systemic toxicity from use of topical corticosteroids. (5.1, 8.4)
- Local adverse reactions with topical corticosteroids may occur more frequently with the use of occlusive dressings, prolonged use, or use of higher potency corticosteroids, including clobetasol propionate. These reactions include; irritation, dryness, acneiform eruptions, hypertrichosis, hypopigmentation, perioral dermatitis, allergic contact dermatitis, secondary infection, striae and miliaria. (5.1, 6.2)

6 ADVERSE REACTIONS

The most common adverse reaction (incidence ≥ 1%) is application site discoloration. (6.1)

To report SUSPECTED ADVERSE REACTIONS, contact Primus Pharmaceuticals Inc. at 480-483-1410 or FDA at 1-800-FDA-1088 or www. FDA.gov/medwatch.

FULL PRESCRIBING INFORMATION

1 INDICATIONS AND USAGE

IMPOYZ Cream 0.025% is indicated for the treatment of moderate to severe plaque psoriasis in patients 18 years of age and older.

2 DOSAGE AND ADMINISTRATION

Apply a thin layer of IMPOYZ Cream to the affected skin areas twice daily and rub in gently and completely. Use IMPOYZ Cream for up to 2 consecutive weeks of treatment. Treatment beyond 2 consecutive weeks is not recommended, and the total dosage should not exceed 50 g per week because of the potential for the drug to suppress the hypothalamic pituitary adrenal (HPA) axis [see Warnings and Precautions (5.1)].

Discontinue IMPOYZ Cream when control is achieved.

Do not use if atrophy is present at the treatment site.

Do not bandage, cover, or wrap the treated skin area unless directed by a physician.

Avoid use on the face, scalp, axilla, groin, or other intertriginous areas.

IMPOYZ Cream is for topical use only. It is not for oral, ophthalmic, or intravaginal use.

Wash hands after each application.

3 DOSAGE FORMS AND STRENGTHS

Cream, 0.025% each gram contains 0.25 mg of clobetasol propionate in a white to off-white cream base.

4 CONTRAINDICATIONS

None.

5 WARNINGS AND PRECAUTIONS

5.1 Effects on the Endocrine System

IMPOYZ Cream can cause reversible hypothalamic-pituitary adrenal (HPA) axis suppression with the potential for glucocorticosteroid insufficiency. This may occur during treatment or after withdrawal of treatment. Because of the potential of systemic absorption, use of topical corticosteroids, including IMPOYZ Cream, may require that patients be evaluated periodically for evidence of HPA axis suppression. Factors that predispose a patient to HPA axis suppression include the use of high-potency steroids, large treatment surface areas, prolonged use, use of occlusive dressings, altered skin barrier, liver failure, and young age.

Evaluation for HPA axis suppression may be done by using the adrenocorticotropic hormone (ACTH) stimulation test. In a trial evaluating the effects of IMPOYZ Cream on the HPA axis, subjects with plaque psoriasis applied IMPOYZ Cream twice daily to at least 20% of involved Body Surface Area (BSA) for 15 days. Abnormal ACTH stimulation tests suggestive of HPA axis suppression were seen in 3 of 24 (12.5%) subjects on IMPOYZ Cream [see Clinical Pharmacology (12.2)]. In another trial to evaluate the effects of IMPOYZ Cream on the HPA axis, subjects with moderate to severe plaque psoriasis applied IMPOYZ Cream twice daily to at least 25% of involved BSA for 28 consecutive days. Abnormal ACTH stimulation test suggestive of HPA axis suppression was seen in 8 of 26 (30.8%) of subjects on IMPOYZ Cream.

If HPA axis suppression is documented, gradually withdraw the drug, reduce the frequency of application, or substitute with a less potent corticosteroid. If signs and symptoms of steroid withdrawal occur, supplemental systemic corticosteroids may be required. Recovery of HPA axis function is generally prompt and complete upon discontinuation of topical corticosteroids.

Systemic effects of topical corticosteroids may also manifest as Cushing’s syndrome, hyperglycemia, and glucosuria. These complications are rare and generally occur after prolonged exposure to larger than recommended doses, particularly with high-potency topical corticosteroids.

Use of more than one corticosteroid-containing product at the same time may increase the total systemic exposure to topical corticosteroids.

Minimize the unwanted risks from endocrine effects by mitigating risk factors favoring increased systemic bioavailability and by using the product as recommended [see Dosage and Administration (2)].

Pediatric patients may be more susceptible to systemic toxicity because of their larger skin surface to body mass ratios [see Use in Specific Populations (8.4)].

5.2 Local Adverse Reactions with Topical Corticosteroids

Local adverse reactions from topical corticosteroids may include atrophy, striae, telangiectasias, burning, itching, irritation, dryness, folliculitis, acneiform eruptions, hypopigmentation, perioral dermatitis, allergic contact dermatitis, secondary infection, and miliaria. These may be more likely to occur with occlusive use, prolonged use, or use of higher potency corticosteroids, including IMPOYZ Cream. Some local adverse reactions by be irreversible.

5.3 Concomitant Skin Infections

Use an appropriate antimicrobial agent if a skin infection is present or develops. If a favorable response does not occur promptly, discontinue use of IMPOYZ Cream until the infection has been adequately treated

5.4 Allergic Contact Dermatitis

Allergic contact dermatitis with corticosteroids is usually diagnosed by observing failure to heal rather than noting a clinical exacerbation. Such an observation should be corroborated with appropriate diagnostic patch testing. If irritation develops, discontinue the topical corticosteroid and institute appropriate therapy.

6 ADVERSE REACTIONS

6.1 Clinical Trials Experience

Because clinical trials are conducted under widely varying conditions, adverse reaction rates observed in the clinical trials of a drug cannot be directly compared to rates in the clinical trials of another drug, and may not reflect the rates observed in practice.

IMPOYZ Cream was evaluated in two randomized, multicenter, prospective, vehicle-controlled clinical trials in subjects with moderate to severe plaque psoriasis. Subjects applied IMPOYZ Cream or vehicle cream twice daily for 14 days. A total of 354 subjects applied IMPOYZ Cream and 178 subjects applied vehicle.

The adverse reaction that occurred in at least 1% of subjects treated with IMPOYZ Cream and at a higher incidence than in subjects treated with vehicle cream was application site discoloration (2% versus 1%).

Less common local adverse events occurring in < 1% of subjects treated with IMPOYZ Cream were application site atrophy, telangiectasia and rash.

6.2 Postmarketing Experience

The following adverse reactions have been identified during post-approval use of clobetasol propionate: striae, irritation, dryness, acneiform eruptions, hypopigmentation, perioral dermatitis, allergic contact dermatitis, secondary infection, hypertrichosis and miliaria. Because these reactions are reported voluntarily from a population of uncertain size, it is not always possible to reliably estimate their frequency or establish a causal relationship to drug exposure.

8 USE IN SPECIFIC POPULATIONS

8.1 Pregnancy

Risk Summary

There are no available data on IMPOYZ Cream in pregnant women to inform a drug-associated risk for adverse development outcomes. Published data report a significantly increased risk of low birthweight with the use of greater than 300 grams of potent or very potent topical corticosteroids during a pregnancy. Advise pregnant women of the potential risk to a fetus and to use IMPOYZ Cream on the smallest area of skin and for the shortest duration possible (see Data). In animal reproduction studies, increased malformations, such as cleft palate and skeletal abnormalities, were observed after subcutaneous administration of clobetasol propionate to pregnant mice and rabbits. No comparisons of animal exposure with human exposure are provided due to minimal systemic exposure noted after topical administration of IMPOYZ Cream [see Clinical Pharmacology (12.3)].

The estimated background risk of major birth defects and miscarriage for the indicated population is unknown. All pregnancies have a background risk or birth defect loss, or other adverse outcomes. In the U.S. general population, the estimated background risk of major birth defects and miscarriage in clinically recognized pregnancies is 2% to 4% and 15% to 20%, respectively.

Data

Human Data

Multiple observational studies found no significant associations between maternal use of topical corticosteroids of any potency and congenital malformations, preterm delivery, or fetal mortality. However, when the dispensed amount of potent or very potent topical corticosteroid exceeded 300 g during the entire pregnancy, use was associated with an increase in low birth weight infants [adjusted RR, 7.74 (95% CI, 1.49-40.11)]. In addition, a small cohort study, in which 28 sub-Saharan women using potent topical corticosteroids (27/28 used clobetasol propionate 0.05%) for skin lightening during pregnancy, noted a higher incidence of low birth weight infants in the exposed group. The majority of exposed subjects treated large areas of the body [a mean quantity of 60 g/month (range, 12-170g)] over long periods of time.

Animal Data

In an embryofetal development study in mice, subcutaneous administration of clobetasol propionate resulted in fetotoxicity at the highest dose tested (1mg/kg) and malformations at the lowest dose tested (0.03 mg/kg). Malformations seen included cleft palate and skeletal abnormalities. In an embryofetal development study in rabbits, subcutaneous administration of clobetasol propionate resulted in malformations at doses of 0.003 and 0.01 mg/kg. Malformations seen included cleft palate, cranioschisis, and other skeletal abnormalities.

8.2 Lactation

Risk Summary

There is no information regarding the presence of clobetasol propionate in breast milk or its effects on the breastfed infant or on milk production. Systemically administered corticosteroids appear in human milk and could suppress growth, interfere with endogenous corticosteroid production, or cause other untoward effects. It is not known whether topical administration of clobetasol propionate could result in sufficient systemic absorption to produce detectable quantities in human milk. The developmental and health benefits of breastfeeding should be considered along with the other’s clinical need for IMPOYZ Cream and any potential adverse effects on the breastfed infant from IMPOYZ Cream or from the underlying maternal condition.

Clinical Considerations

To minimize potential exposure to the breastfed infant via breast milk, use IMPOYZ Cream on the smallest area of skin and for the shortest duration possible while breastfeeding. Advise breastfeeding women not to apply IMPOYZ Cream directly to the nipple and areola to avoid direct infant exposure.

8.4 Pediatric Use

The safety and effectiveness of IMPOYZ Cream in patients younger than 18 years of age have not been established; therefore, use in children younger than 18 years is not recommended. Because of a higher ratio of skin surface area to body mass, pediatric patients are at a greater risk than adults of systemic toxicity, including HPA axis suppression when treated with topical drugs [see Warnings and Precautions (5.1)].

Rare systemic toxicities such as Cushing’s syndrome, linear growth retardation, delayed weight gain, and intracranial hypertension have been reported in pediatric patients, especially those with prolonged exposure to large doses of high potency topical corticosteroids.

Local adverse reactions including striae and skin atrophy have also been reported with use of topical corticosteroids in pediatric patients.

Avoid use of IMPOYZ Cream in the treatment of diaper dermatitis.

8.5 Geriatric Use

Clinical studies of IMPOYZ Cream did not include sufficient numbers of subjects aged 65 and over to determine whether they respond differently from younger subjects. Other reported clinical experience with topical corticosteroids has not identified differences in responses between the elderly and younger patients.

11 DESCRIPTION

IMPOYZ (clobetasol propionate) Cream, 0.025% for topical use contains clobetasol propionate, a synthetic and fluorinated corticosteroid. Chemically, clobetasol propionate is 21-chloro-9-fluoro-11β-hydroxy-16 β-methyl-3,20-dioxopregna-1,4-dien-17-yl propanoate, and it has the following structural formula.

Clobetasol propionate has a molecular formula of C25H32CIFO5 and a molecular weight of 467. It is a white to cream-colored crystalline powder practically insoluble in water.

Each gram of IMPOYZ Cream contains 0.25 mg clobetasol propionate. It is an oil-in-water emulsion intended for topical application and contains the following inactive ingredients: butylated hydroxytoluene, cetostearyl alcohol, cyclomethicone, diethylene glycol monoethyl ether, glyceryl stearate and PEG 100 stearate, isopropyl myristate, methyl paraben, propyl paraben. purified water and white wax.

12 CLINICAL PHARMACOLOGY

12.1 Mechanism of Action

Corticosteroids play a role in cellular signaling, immune function, inflammation, and protein regulation; however, the precise mechanism of action in corticosteroid responsive dermatoses is unknown. The contribution to efficacy by individual components of the vehicle has not been established.

12.2 Pharmacodynamics

Vasoconstrictor Assay

IMPOYZ Cream, 0.025% is in the high range of potency as demonstrated in vasoconstrictor studies in healthy subjects when compared with other topical corticosteroids. However, similar blanching scores do not necessarily imply therapeutic equivalence.

Hypothalamic-Pituitary-Adrenal (HPA) Axis Suppression:

HPA axis suppression was evaluated in a clinical trial in adult subjects (N=24) with moderate to severe plaque psoriasis involving a mean BSA of 26.5 +8.6%. Treatment consisted of twice daily application of IMPOYZ Cream, 0.025% for 15 days. Adrenal suppression, as indicated by a 30-minute post-stimulation cortisol level ≤18 mcg/dL, was observed in 3 out of 24 subjects (12.5%) after 15 days.

12.3 Pharmacokinetics

Topical corticosteroids can be absorbed from intact healthy skin. The extent of percutaneous absorption of topical corticosteroids is determined by many factors, including the product formulation and the integrity of the epidermal barrier. Occlusion, inflammation, and/or other disease processes in the skin may also increase percutaneous absorption. Once absorbed through the skin, topical corticosteroids are metabolized, primarily in the liver, and are then excreted by the kidneys. Some corticosteroids and their metabolites are also excreted in the bile.

In a pharmacokinetic study in 24 adult male and female subjects with moderate to severe psoriasis were treated twice daily for 15 days with a mean dose of approximately 3.7 g of IMPOYZ Cream, 0.025% per application to a mean BSA of 26.5 ± 8.6%. On day 15, the mean + SD pre-treatment and post-treatment systemic concentrations of clobetasol propionate were 50.7 ± 96.0 pg/mL and 56.3 ± 104.7 pg/mL, respectively.

13 NONCLINICAL TOXICOLOGY

13.1 Carcinogenesis, Mutagenesis, Impairment of Fertility

Long term animal studies have not been performed to evaluate the carcinogenic potential of clobetasol propionate cream.

In a 13-week repeat dose toxicity study in rats, topical administration of clobetasol propionate cream, 0.001, 0.005 and 0.025% at corresponding doses of 0.004, 0.02 and 0.1 mg/kg/day resulted in corticosteroid class-related systemic effects such as reductions in body weight gain, reductions in total leukocytes and individual white cells, decrease in weight of adrenals, thymus, spleen, liver and lung. Histologically, there were decreased hematopoiesis in the bone marrow, thymic atrophy and mast cell infiltration of the mesenteric lymph nodes. All these effects were indicative of severe immune suppression consistent with long-term exposure to corticosteroids. A no observable adverse effect level (NOAEL) was determined to be clobetasol propionate cream, 0.001% (0.004 mg/kg/day) in male rats while a NOAEL could not be determined in females. The clinical relevance of the findings in animals to humans is not clear, but sustained glucocorticoid-related immune suppression may increase the risk of infection and possibly the risk of carcinogenesis.

Clobetasol propionate was not mutagenic in three different test systems: the Ames test, the Saccharomyces cerevisiae gene conversion assay, and the E. coli B WP2 fluctuation test.

Fertility studies conducted in the rat following subcutaneous administration of clobetasol propionate at dosage levels up to 0.05 mg/kg/day revealed that females exhibited an increase in the number of resorbed embryos and a decrease in the number of living fetuses at the highest dose.

14 CLINICAL STUDIES

Two double-blind, randomized, vehicle-controlled trials evaluated 532 subjects aged 18 years and older with moderate to severe plaque psoriasis (IGA 3 or 4 and BSA > 3%). Subjects were treated twice daily with IMPOYZ Cream or vehicle cream for 14 days. The primary endpoint was the proportion of subjects who achieved treatment success at Day 15, where treatment success was defined as an IGA score of 0 (clear) or 1 (almost clear) with at least a 2-grade reduction from baseline. The proportion of subjects who achieved treatment success was also assessed at Day 8

Table 1 presents the efficacy results at Day 8 and Day 15

Table 1. Treatment Success* Results

 | Trial 1 |  | Trial 2
 | IMPOYZ (N=178) | Vehicle (N=89) | IMPOYZ (N=176) | Vehicle (N=89)
Day 15 (primary endpoint) | 30.2% | 9.0% | 30.1% | 9.7%
Day 8 (secondary endpoint) | 15.7% | 5.6% | 14.2% | 1.6%
*Treatment success is defined as an IGA score of 0 (clear) or 1 (almost clear) with at least a 2-grade reduction from baseline.

16 HOW SUPPLIED/STORAGE AND HANDLING

16.1 How Supplied

IMPOYZ Cream, 0.025% is a white off-white cream, supplied as follows:

100 g aluminum tube NDC 68040-713-38

16.2 Storage

Store at 20°C-25°C (68°F-77°F), excursions permitted to 15°C-30°C (59°F-86°F) [see USP Controlled Room Temperature]. Do not freeze.

17 PATIENT COUNSELING INFORMATION

Advise the patient to read the FDA-approved patient labeling (Patient Information)

Pregnancy

Advise pregnant women of the potential risk to a fetus and to use IMPOYZ Cream on the smallest area of skin and for the shortest duration possible [see Use in Specific Populations (8.1)].

Lactation

Advise a woman to use IMPOYZ cream on the smallest area of skin and for the shortest duration possible while breastfeeding. Advise breastfeeding women not to apply IMPOYZ Cream directly to the nipple and areola to avoid direct infant exposure [see Use in Specific Populations (8.2)].

Important Administration Instructions

Instruct patients to discontinue IMPOYZ Cream when psoriasis is controlled. IMPOYZ Cream should not be used for longer than 2 weeks. Advise patients to contact the physician if no improvement is seen within 2 weeks. Inform patients that total dosage should not exceed 50 grams per week [see Dosage and Administration (2)].

Instruct patients to avoid bandaging, wrapping or otherwise occluding the treatment area(s) unless directed by physician. Advise patients to avoid use on the face, scalp, groin, or axillae [see Dosage and Administration (2)].

Inform patients that IMPOYZ Cream is for external use only. Advise patients that IMPOYZ Cream is not for ophthalmic, oral or intravaginal use. Patients should wash their hands after applying the medication [see Dosage and Administration (2)].

Do not use other corticosteroid-containing products while using IMPOYZ Cream.

Effects on Endocrine System

IMPOYZ Cream may cause HPA axis suppression. Advise patients that use of topical corticosteroids, including IMPOYZ Cream, may require periodic evaluation for HPA axis suppression. Topical corticosteroids may have other endocrine effects. Concomitant use of multiple corticosteroid-containing products may increase the total systemic exposure to topical corticosteroids. Patients should inform their physician(s) that they are using IMPOYZ Cream if surgery is contemplated [see Warnings and Precautions (5.1)].

Local Adverse Reactions

Informed patients that topical corticosteroids may cause local adverse reactions, some of which may be irreversible. These reactions may be more likely to occur with occlusive use, prolonged use or use of higher potency corticosteroids, including IMPOYZ Cream [see Warnings and Precautions (5.2)]. Patients should report any sign of local or systemic adverse reactions to their physician.

Manufactured by DPT Laboratories Ltd. San Antonio, TX 78215
For Primus Pharmaceuticals, Inc., Scottsdale AZ 85253
IMPOYZ is a registered trademark of Primus Pharmaceuticals, Inc.

www.primusrx.com
Revised: 04/2021

INSTRUCTIONS FOR USE

PATIENT INFORMATION
IMPOYZ® (Im-poise)
(clobetasol propionate)
Cream, 0.025%

Important: IMPOYZ Cream is for use on the skin only. Do not get IMPOYZ Cream near or in your eyes, mouth, or vagina.

What is IMPOYZ Cream?

IMPOYZ Cream is a prescription corticosteroid medicine used to treat moderate to severe plaque psoriasis in people 18 year of age and older.

It is not known if IMPOYZ Cream is safe and effective in children under 18 years of age. IMPOYZ Cream is not recommended for use in children under 18 years of age.

Before using IMPOYZ Cream, tell your doctor about all of your medical conditions, including if you:

- have thinning of the skin (atrophy) at the treatment site.
- have a skin infection. You may need medicine to treat the skin infection before using IMPOYZ Cream.
- have diabetes.
- have adrenal gland problems.
- plan to have surgery.
- liver problems
- are pregnant or plan to become pregnant. It is not known if IMPOYZ Cream will harm your unborn baby. If you use IMPOYZ Cream during pregnancy, use IMPOYZ Cream on the smallest area of skin and for the shortest time needed.
- are breastfeeding or plan to breastfeed. It is not known if IMPOYZ Cream passes into breast milk. Breastfeeding women should use IMPOYZ Cream on the smallest area of skin and for the shortest time needed while breastfeeding. Do not apply IMPOYZ Cream directly to the nipple and areola to avoid contact with your baby.

Tell your doctor about all the medicines you take, including prescription and over-the-counter medicines, vitamins, and herbal supplements. Especially tell your doctor if you take other corticosteroid medicines by mount or use other products on your skin that contain corticosteroids.

Do not use other product containing a corticosteroid medicine with IMPOYZ Cream without talking to your doctor first.

How should I use IMPOYZ Cream?

- Use IMPOYZ Cream exactly as your doctor tells you to use it
- Your doctor should tell you how much IMPOYZ Cream to use and where to apply it.
- Apply a thin layer of IMPOYZ Cream to the affected skin areas 2 times each day and rub in gently and completely.
- Use IMPOYZ Cream for the shortest amount of time needed to treat your plaque psoriasis. Tell your doctor if your skin condition is not getting better after 2 weeks for using IMPOYZ. Do not use IMPOYZ Cream for longer than 2 weeks in a row.
- Do not use IMPOYZ Cream on your face, scalp, underarms (armpits), groin, or areas where your skin may touch or rub together.
- Do not use IMPOYZ Cream if thinning of the skin atrophy is present at the treatment site.
- Do not bandage, cover, or wrap the treated skin area unless your doctor tells you to.
- Wash your hand after you apply IMPOYZ Cream.
- See your doctor regularly to check your symptom and side effects while using IMPOYZ Cream.

What are the possible side effects of IMPOYZ Cream?

IMPOYZ Cream may cause serious side effects, including:

- Symptoms of a disorder where the adrenal gland does not make enough of certain hormones (adrenal insufficiency) during treatment or after stopping treatment with IMPOYZ Cream.Your doctor may do blood tests to check for adrenal gland problems during treatment with IMPOYZ Cream.
- Cushing syndrome, a condition that can happen when your body is exposed to too much of the hormone cortisol. Your doctor may do tests to check for this.
- High blood sugar (hyperglycemia) or diabetes mellitus that has not been diagnosed can happened with treatment.Your doctor may do tests to check for this.
- Skin reactions at the treated skin site. Tell your doctor if you get any skin reactions or skin infections.
- Effects on growth and weight in children.

The most common side effect of IMPOYZ Cream includes discoloration of the treated site. This is not the only possible side effect of IMPOYZ Cream.

Call your doctor for medical advice about side effects. You may report side effects to FDA at 1-800-FDA-1088.

How should I store IMPOYZ Cream?

- Store IMPOYZ Cream between 68°F to 77°F (20°C to 25°C).
- Do not freeze.
- Throw away (discard) any unused IMPOYZ Cream after 2 weeks.

Keep IMPOYZ Cream and all medicines out of the reach of children.

General information about the safe and effective use of IMPOYZ Cream.

Medicines are sometimes prescribed for purposes other than those listed in the Patient Information leaflet. Do not use IMPOYZ Cream for a condition for which it was not prescribed. Do not give IMPOYZ Cream to other people even if they have the same symptoms that you have. It may harm them. You can ask your pharmacist or doctor for information about IMPOYZ Cream that is written for health professionals.

What are the ingredients in IMPOYZ Cream?

Active ingredients: clobetasol propionate

Inactive ingredients: butylated hydroxytoluene, cetostearyl alcohol, cyclomethicone, diethylene glycol monoethyl ether, glyceryl stearate and PEG 100 stearate, isopropyl myristate, methyl paraben, propyl paraben, purified water and white wax.

Manufactured by DPT Laboratories Ltd. San Antonio, TX 78215

For Primus Pharmaceuticals, Inc. Scottsdale AZ 85253 Revised 04/2021

This patient information has been approved by the U.S. Food and Drug Administration Issued 11/2017

PRINCIPAL DISPLAY PANEL - NDC: 68040-713-38 - 100 g Tube Label

NDC 68040-713-38

Net Wt. 100 g

Rx only

impoyz®

(clobetasol propionate)

Cream, 0.025%

FOR TOPICAL USE ONLY

NOT FOR ORAL, OPHTHALMIC OR INTRAVAGINAL USE

PRINCIPAL DISPLAY PANEL - NDC: 68040-713-38 - 100 g Carton Label

NDC 68040-713-38

Net Wt. 100 g

Rx only

impoyz®

(clobetasol propionate)

Cream, 0.025%

FOR TOPICAL USE ONLY

NOT FOR ORAL, OPHTHALMIC OR INTRAVAGINAL USE

PRINCIPAL DISPLAY PANEL - NDC: 68040-713-44 - 2.5 g Sample Tube Label

NDC 68040-713-44

SAMPLE
Not for individual sale

2.5 g

Rx only

impoyz®

(clobetasol propionate)

Cream, 0.025%

FOR TOPICAL USE ONLY

PRINCIPAL DISPLAY PANEL - NDC: 68040-713-44 - 2.5 g Sample Carton Label

NDC 68040-713-44

Rx only

Sample - Not for individual sale
Contains twenty individual 2.5 g tubes

impoyz®

(clobetasol propionate)

Cream, 0.025%

FOR TOPICAL USE ONLY

NOT FOR ORAL, OPHTHALMIC OR INTRAVAGINAL USE